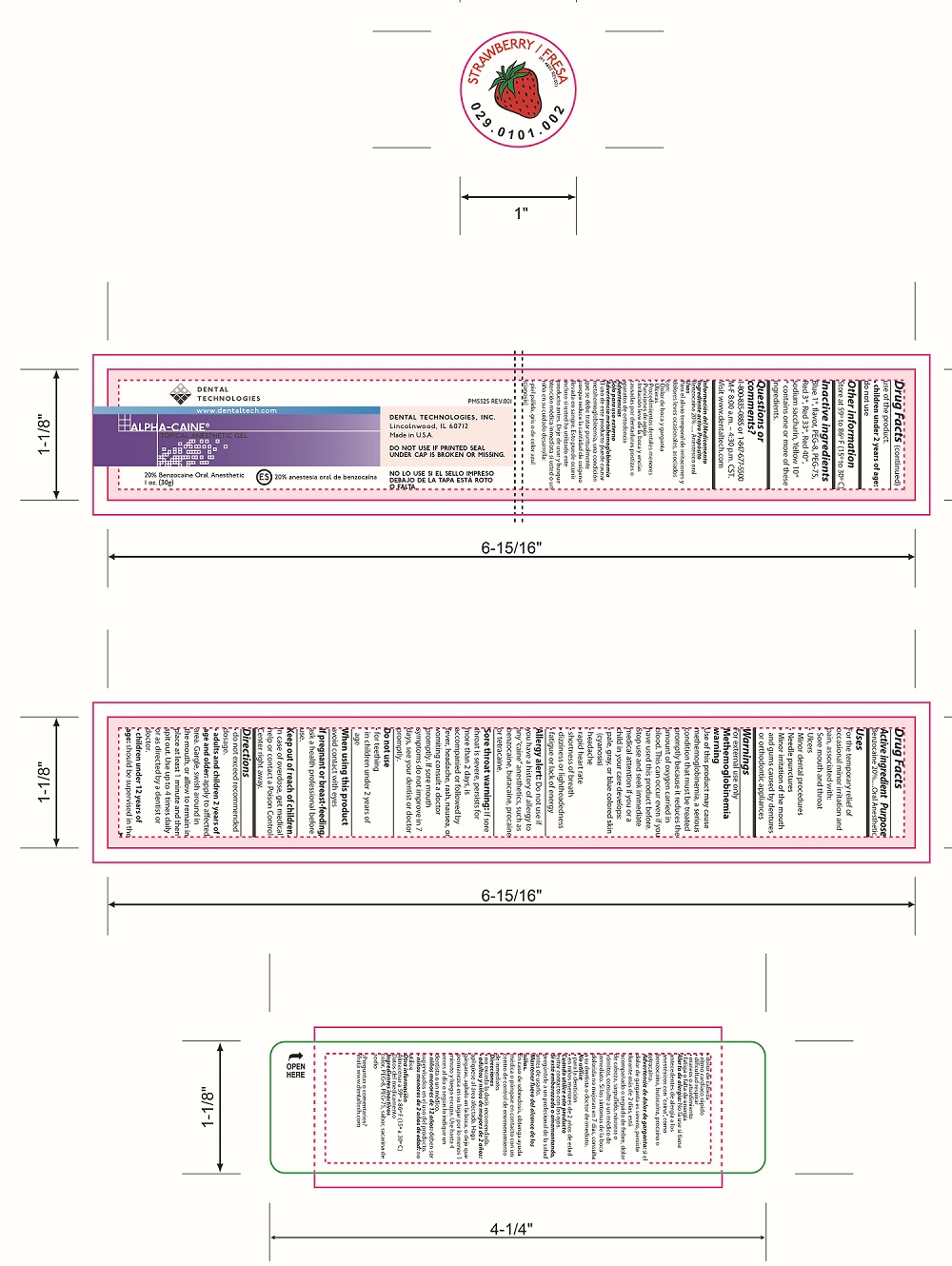 DRUG LABEL: Alpha-Caine
NDC: 55346-2901 | Form: GEL
Manufacturer: Dental Technologies, Inc.
Category: otc | Type: HUMAN OTC DRUG LABEL
Date: 20251104

ACTIVE INGREDIENTS: BENZOCAINE 200 mg/1 g
INACTIVE INGREDIENTS: POLYETHYLENE GLYCOL 400; POLYETHYLENE GLYCOL 3350; SACCHARIN SODIUM; FD&C RED NO. 40

Alpha-Caine Drug Facts, Strawberry

Active ingredient

Benzocaine 20%

Purpose

Oral Anesthetic

Uses

For the temporary relief of occasional minor irritation and pain, associated with:

- Sore mouth and throat
- Ulcers
- Minor dental procedures
- Needle punctures
- Minor irritation of the mouth and gums caused by dentures or orthodontic appliances

Warnings

For external use only

Methemoglobinemia warning

Use of this product may cause methemoglobinemia, a serious condition that must be treated promptly because it reduces the amount of oxygen carried in blood. This can occur even if you have used this product before. Stop use and seek immediate medical attention if you or a child in your care develops:

- pale, gray or blue colored skin (cyanosis)
- headache
- rapid heart rate
- shortness of breath
- dizziness or lightheadedness
- fatigue or lack of energy

Allergy alert:

Do not use if you have a history of allergy to any “caine” anesthetics, such as benzocaine, butacaine, procaine or tetracaine.

Sore throat warning:

If sore throat is severe, persists for more than 2 days, is accompanied or followed by fever, headache, rash, nausea, or vomiting consult a doctor promptly. If sore mouth symptoms do not improve in 7 days, see your dentist or doctor promptly.

Do not use

- for teething
- in children under 2 years of age

When using this product

avoid contact with eyes

If pregnant or breast-feeding,

ask a health professional before use.

Keep out of reach of children.

In case of overdose, get medical help or contact Poison Control Center right away.

Directions

do not exceed recommended dosage.

- adults and children 2 years of age and older: apply to affected area. Gargle, swish around in the mouth, or allow to remain in place at least 1 minute and then spit out. Use up to 4 times daily or as directed by dentist or doctor.
- children under 12 years of age: should be supervised in the use of the product.
- children under 2 years of age: do not use

Other information

Store at 59° to 86º F (15º to 30º C)

Inactive ingredients

Blue 1*, flavor, PEG-8, PEG-75, Red 3*, Red 33*, Red 40*, sodium saccharin, Yellow 10*

*contains one or more of these ingredients.

Questions or comments?

1-800-835-0885 or 1-847-677-5500 M-F 8:00 a.m. – 4:30 p.m. CST.

Visit www.dentaltech.com

Principal Display Panel

DENTAL

TECHNOLOGIES

www.dentaltech.com

ALPHA-CAINE

TOPICAL ANESTHETIC GEL

DENTAL TECHNOLOGIES, INC.

Lincolnwood, IL 60712

Made in U.S.A.

DO NOT USE IF PRINTED SEAL UNDER CAP IS BROKEN OR MISSING.

20% Benzocaine Oral Anesthetic

1oz. (30g)